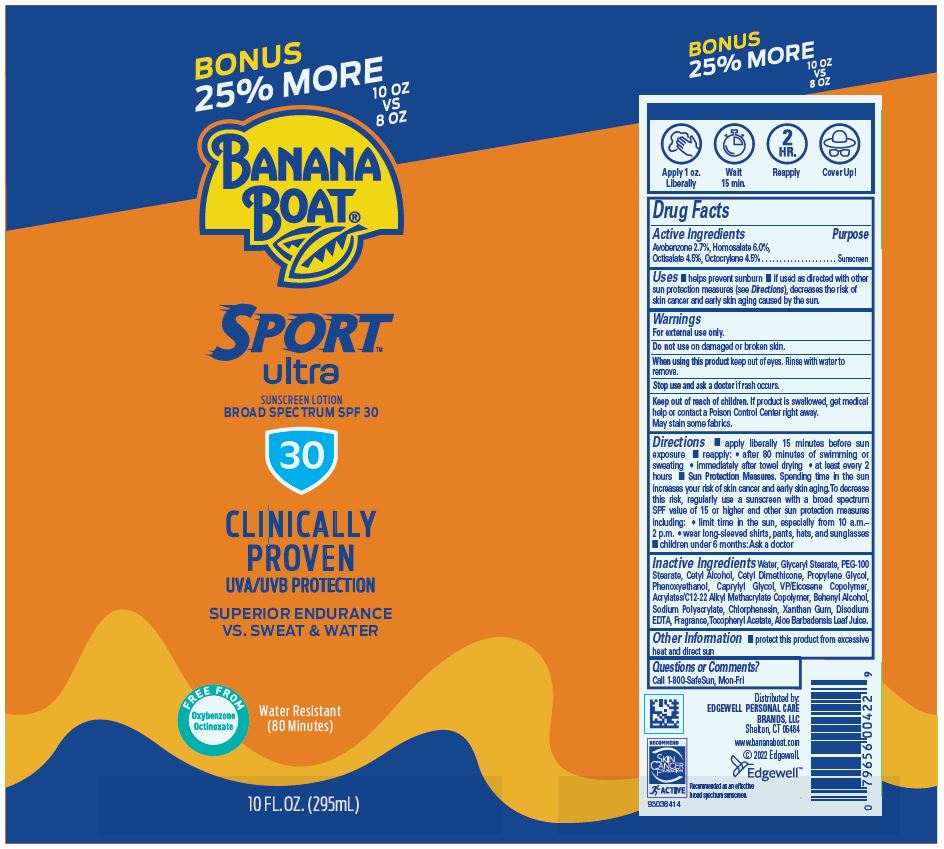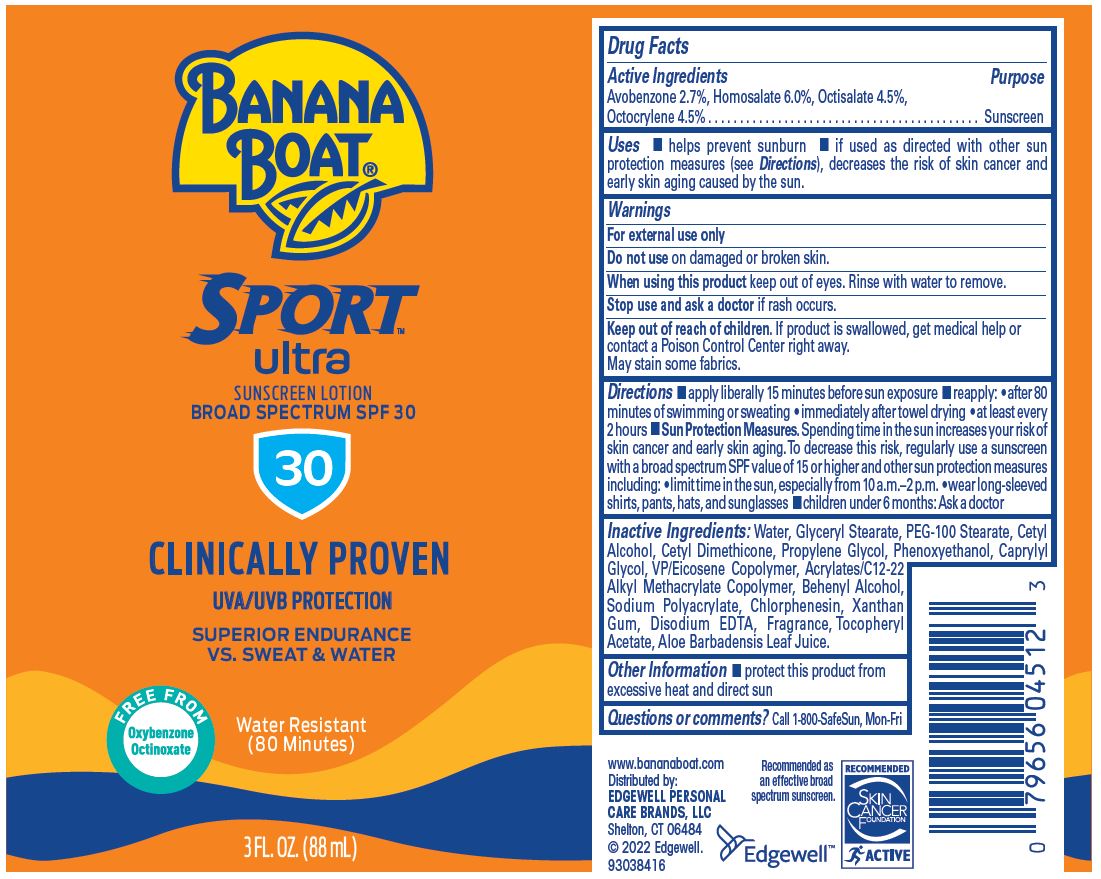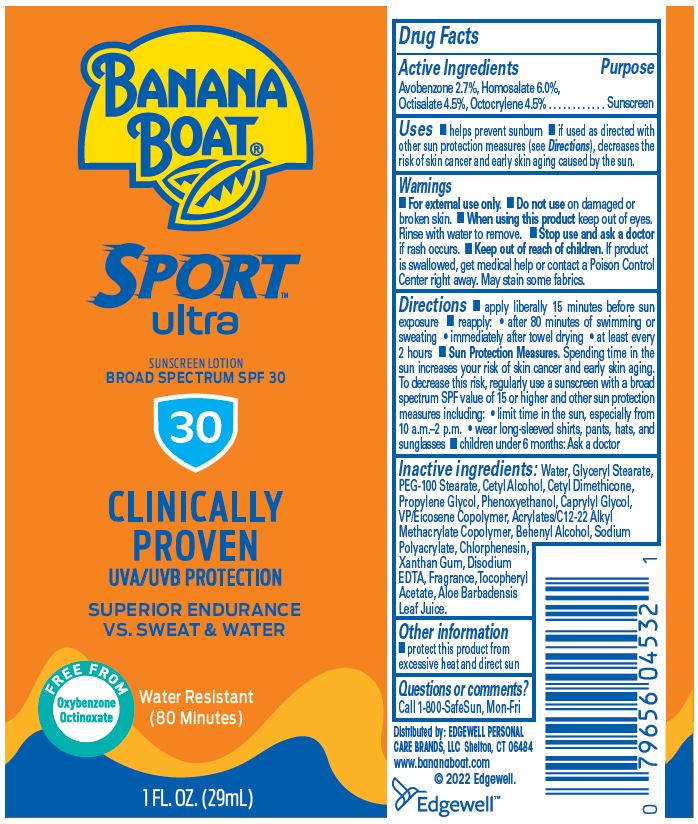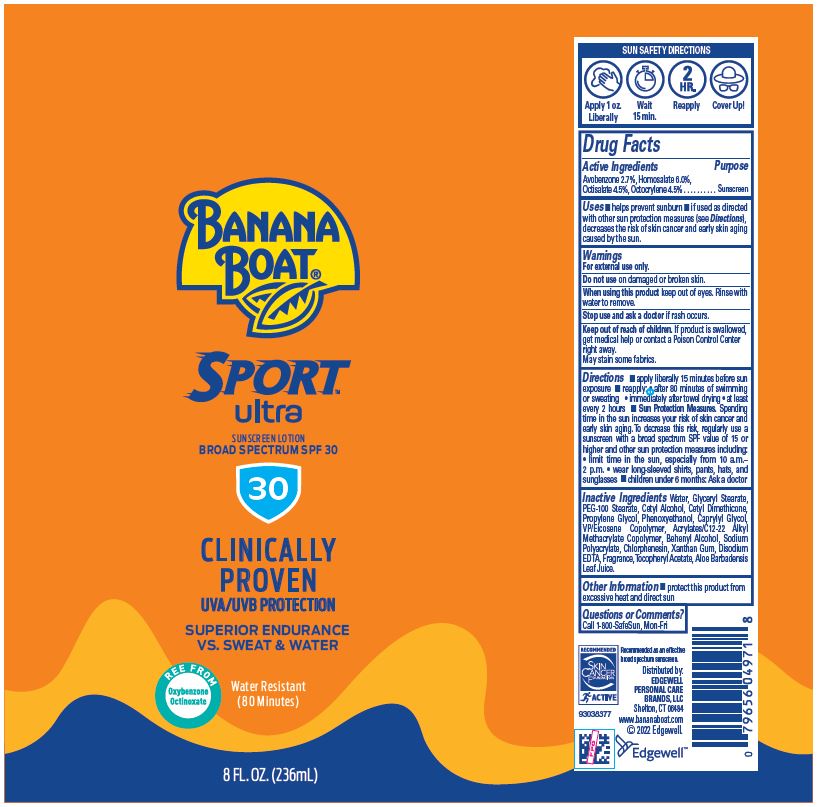 DRUG LABEL: Banana Boat Ultra Sport Sunscreen Broad Spectrum SPF 30
NDC: 63354-470 | Form: LOTION
Manufacturer: Edgewell Personal Care Brands LLC
Category: otc | Type: HUMAN OTC DRUG LABEL
Date: 20251202

ACTIVE INGREDIENTS: OCTISALATE 4.5 g/100 g; OCTOCRYLENE 4.5 g/100 g; AVOBENZONE 2.7 g/100 g; HOMOSALATE 6 g/100 g
INACTIVE INGREDIENTS: WATER; CHLORPHENESIN; CETYL DIMETHICONE 150; PHENOXYETHANOL; VINYLPYRROLIDONE/EICOSENE COPOLYMER; CAPRYLYL GLYCOL; CETYL ALCOHOL; SODIUM POLYACRYLATE (8000 MW); GLYCERYL 1-STEARATE; XANTHAN GUM; EDETATE DISODIUM ANHYDROUS; .ALPHA.-TOCOPHEROL ACETATE; ALOE VERA LEAF; PROPYLENE GLYCOL; DOCOSANOL; PEG-100 STEARATE

Active Ingredients

Avobenzone 2.7%, Homosalate 6.0%, Octisalate 4.5%, Octocrylene 4.5%

Purpose

Sunscreen

Uses

• helps prevent sunburn • if used as directed with other sun protection measures (see Directions), decreases the risk of skin cancer and early skin aging caused by the sun

Warnings

For external use only.

May stain some fabrics

Do not use

on damaged or broken skin

When using this product

keep out of eyes. Rinse with water to remove.

Stop use and ask a doctor

if rash occurs

Keep out of reach of children

If product is swallowed, get medical help or contact a Poison Control Center right away.

Directions

• apply liberally 15 minutes before sun exposure • reapply: • after 80 minutes of swimming or sweating • immediately after towel drying • at least every 2 hours • Sun Protection Measures. Spending time in the sun increases your risk of skin cancer and early skin aging. To decrease this risk, regularly use a sunscreen with a broad spectrum SPF of 15 or higher and other sun protection measures including: • limit time in the sun, especially from 10 a.m. - 2 p.m. • wear long-sleeved shirts, pants, hats, and sunglasses • children under 6 months: Ask a doctor

Inactive Ingredients

Water, Glyceryl Stearate, PEG-100 Stearate, Cetyl Alcohol, Cetyl Dimethicone, Propylene Glycol, Phenoxyethanol, Caprylyl Glycol, VP/Eicosene Copolymer, Acrylates/C12-22 Alkyl Methacrylate Copolymer, Behenyl Alcohol, Sodium Polyacrylate, Chlorphenesin, Xanthan Gum, Disodium EDTA, Fragrance, Tocopheryl Acetate, Aloe Barbadensis Leaf Juice

Other information

• protect this product from excessive heat and direct sun

Questions or Comments?

Call 1-800-SafeSun, Mon-Fri

Primary Display Panel

BANANA
BOAT®
SPORT™
ultra
SUNSCREEN LOTION
BROAD SPECTRUM SPF 30
30
CLINICALLY
PROVEN
UVA/UVB PROTECTION
SUPERIOR ENDURANCE
VS. SWEAT & WATER
FREE FROM
Oxybenzone
Octinoxate
Water Resistant
(80 Minutes)
1 FL. OZ. (29mL)

BANANA
BOAT®
SPORT™
ultra
SUNSCREEN LOTION
BROAD SPECTRUM SPF 30
30
CLINICALLY
PROVEN
UVA/UVB PROTECTION
SUPERIOR ENDURANCE
VS. SWEAT & WATER
FREE FROM
Oxybenzone
Octinoxate
Water Resistant
(80 Minutes)
3 FL. OZ. (88mL)

BANANA
BOAT®
SPORT™
ultra
SUNSCREEN LOTION
BROAD SPECTRUM SPF 30
30
CLINICALLY
PROVEN
UVA/UVB PROTECTION
SUPERIOR ENDURANCE
VS. SWEAT & WATER
FREE FROM
Oxybenzone
Octinoxate
Water Resistant
(80 Minutes)
8 FL. OZ. (236mL)

BONUS
25% MORE
10 OZ
VS
8 OZ
BANANA
BOAT®
SPORT™
ultra
SUNSCREEN LOTION
BROAD SPECTRUM SPF 30
30
CLINICALLY
PROVEN
UVA/UVB PROTECTION
SUPERIOR ENDURANCE
VS. SWEAT & WATER
FREE FROM
Oxybenzone
Octinoxate
Water Resistant
(80 Minutes)
10 FL. OZ. (295mL)